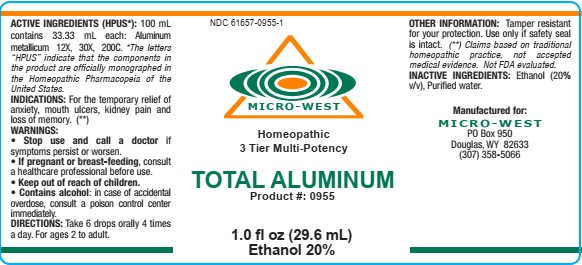 DRUG LABEL: Total Aluminum
NDC: 61657-0955 | Form: LIQUID
Manufacturer: White Manufacturing Inc. DBA Micro-West
Category: homeopathic | Type: HUMAN OTC DRUG LABEL
Date: 20210121

ACTIVE INGREDIENTS: ALUMINUM 12 [hp_X]/30 mL
INACTIVE INGREDIENTS: ALCOHOL

DRUG FACTS

Manufactured for

Micro-West

P.O. Box 950

Douglas WY

1-307-358-5066

Directions

Directions: Take 6 drops orally, 4 times a day. For ages 2 to adult

INDICATIONS

INDICATIONS: For the temporary relief of anxiety, mouth ulcers, kidney pain and loss of memory

Active Ingredients

I ngredients: ALUMIN MET 12X, 30X,200C, 1M

WARNING

WARNING: Stop use and call a doctor if symptoms persist or worsen. If pregnant or breast-feeding, consult a healthcare professional before use. Contains alcohol: in case of accidental overdose, consult a poison control center immediately.

OTHER SAFETY INFORMATION

OTHER INFORMATION: Tamper resistant for your protection. Use only if safety seal is intact.

Keep out of reach of children

Inactive Ingredient

Inactive ingredients: Alcohol (20%, v/v), Purified water

Purpose

Temporary relief of anxiety, mouth ulcers, kidney pain and loss of memory

Label

NDC 61657-0955-1

MICRO-WEST

Homeopathic

3 Tier Multi-Potency

TOTAL ALUMINUM

Product #: 0955

1.0 fl oz (29.6 mL)

Ethanol 20%